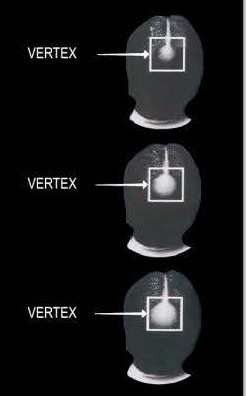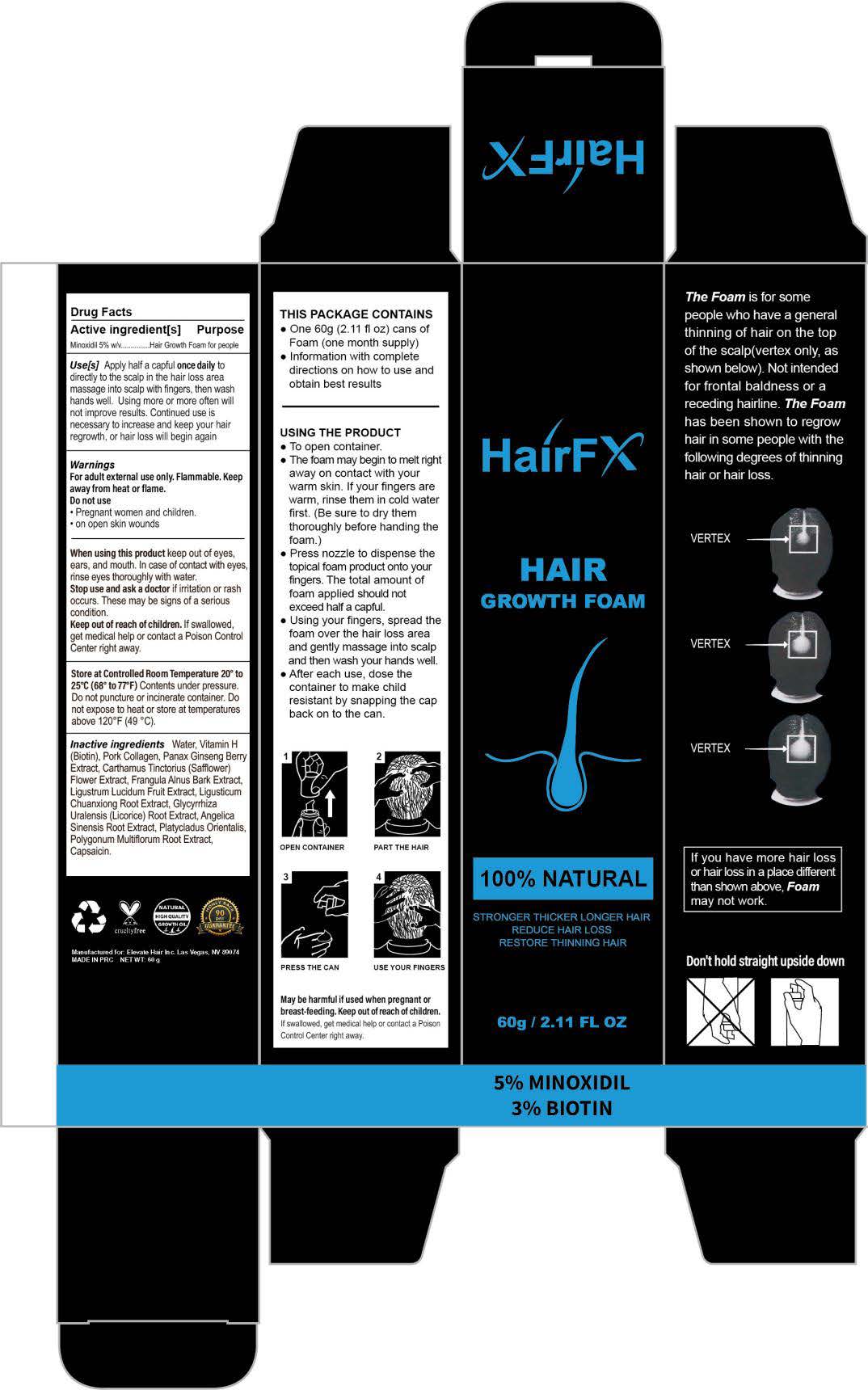 DRUG LABEL: HAIRFX HAIR GROWTH FOAM
NDC: 81653-003 | Form: AEROSOL, FOAM
Manufacturer: Guangzhou Jianyuan Biological Technology.Co.,Ltd
Category: otc | Type: HUMAN OTC DRUG LABEL
Date: 20250116

ACTIVE INGREDIENTS: MINOXIDIL 5 g/100 g
INACTIVE INGREDIENTS: WATER; SAFFLOWER; CAPSAICIN; LIGUSTICUM SINENSE SUBSP. CHUANXIONG ROOT; LIGUSTRUM LUCIDUM FRUIT; ANGELICA SINENSIS ROOT; REYNOUTRIA MULTIFLORA ROOT; BIOTIN; PORK COLLAGEN; PANAX GINSENG FRUIT; FRANGULA ALNUS BARK; GLYCYRRHIZA URALENSIS ROOT; PLATYCLADUS ORIENTALIS WHOLE

81653-003 Update

Active ingredient

Minoxidil 5%

PURPOSE

STRONGER THICKER LONGER HAIR
REDUCE HAIR LOSS
RESTORE THINNING HAIR
The Foam is for somepeople who have a general thinning of hair on the top of the scalp(vertex only, asshown below). Not intendedfor frontal baldness or areceding hairline. The Foamhas been shown to regrowhair in some people with thefollowing degrees of thinninghair or hair loss.

lf you have more hair loss or hair loss in a place different than shown above, Foam may not work.

lnactive ingredients

Water, Vitamin H (Biotin), Pork Collagen. Panax Ginseng Berry Extract, Carthamus Tinctorius (Safflower) Flower Extract, Frangula Alnus Bark Extract, Ligustrum Lucidum Fruit Extract, Ligusticum Chuanxiong Root Extract, Glycyrrhiza Uralensis (Licorice) Root Extract, Angelica Sinensis Root Extract, Platycladus Orientalis, Polygonum Multiflorum Root Extract, Capsaicin

INDICATIONS AND USAGE

for hair loss

Apply half a capful once daily to directly to the scalp in the hair loss area massage into scalp with fingers. then wash hands well.Using more or more often will not improve results. Continued use is necessary to increase and keep your hair regrowth, or hair loss will begin again

Keep out of reach of children.lf swallowed, get medical help or contact a Poison Control Center right away.

WARNINGS

For adult external use only. Flammable. Keep away fromheat or flame.
Do not use
·Pregnant women and children.
·on open skin wounds

When using this product keep out of eyes, ears, andmouth. In case of contact with eyes, rinse eyes thoroughlywith water.
Stop use and ask a doctor if irritation or rash occurs.These may be signs of a serious condition.

ROUTE, METHOD AND FREQUENCY OF ADMINISTRATION

USING THE PRODUCT
To open container.
The foam may begin to melt right away on contact with your
warm skin. If your fingers arewarm, rinse them in cold water first.(Be sure to dry them thoroughly before handing thefoam.)
Press nozzle to dispense the topical foam product onto your fingers. The total amount of foam applied should not exceed half a capful.
Using your fingers, spread the foam over the hair loss area
and gently massage into scalp and then wash your hands well. After each use, dose the container to make child resistant by snapping the cap back on to the can.

other information

Store at Controlled Room Temperature 20 °C to25 °C(68°Fto 77°F)
Contents under pressure.Do not puncture or incinerate container. Do not expose to heat or store at temperatures above 120°F(49 °C).

Don't hold straight upside down

Do not use
- Pregnant women and children.
- on open skin wounds
when using this product
keep out of eyes,ears, and mouth. ln case of contact with eyes, rinse eyes thoroughly with water.
Stop use and ask a doctor
if irritation or rashoccurs.These may be signs of a serious condition.
Keep out of reach of children.
If swallowed, get medical help or contact a Poison ControlCenter right away.

DOSAGE AND ADMINISTRATION

THIS PACKAGE CONTAINS. One 60g (2.11 fl oz) cans of Foam (one month supply)

Apply half a capful once daily to directly to the scalp in the hair loss area massage into scalp with fingers